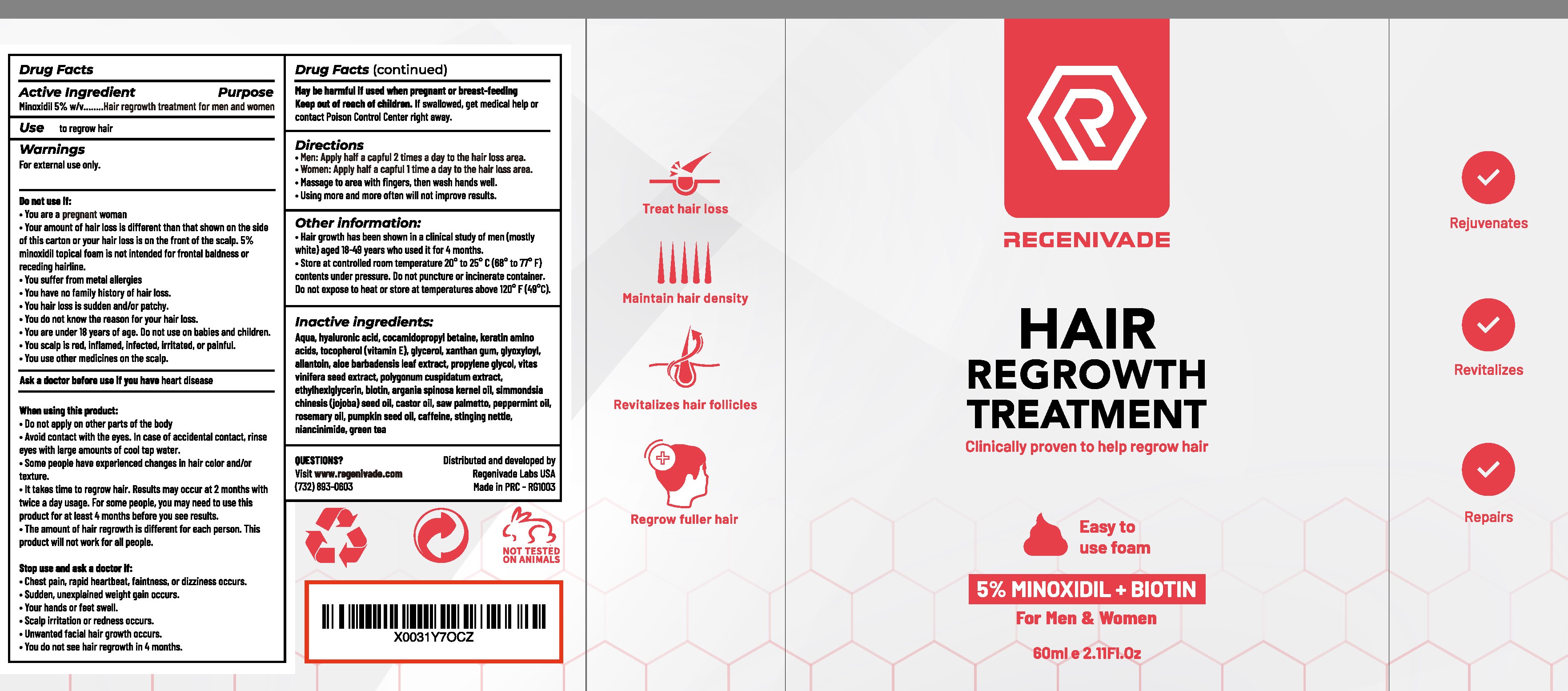 DRUG LABEL: Regenivade Hair Growth Foam
NDC: 81653-007 | Form: LIQUID
Manufacturer: Guangzhou Jianyuan Biological Technology.Co.,Ltd
Category: otc | Type: HUMAN OTC DRUG LABEL
Date: 20250116

ACTIVE INGREDIENTS: MINOXIDIL 5 mg/1 mL
INACTIVE INGREDIENTS: PUMPKIN SEED OIL; NIACINAMIDE; PEPPERMINT OIL; COCAMIDOPROPYL BETAINE; ALLANTOIN; VITIS VINIFERA SEED; GREEN TEA LEAF; TEA TREE OIL; HYALURONIC ACID; CAFFEINE; URTICA DIOICA; JOJOBA OIL; XANTHAN GUM; REYNOUTRIA JAPONICA LEAF; SAW PALMETTO; ROSEMARY OIL; ETHYLHEXYLGLYCERIN; PROPYLENE GLYCOL; WATER; HAIR KERATIN AMINO ACIDS; .ALPHA.-TOCOPHEROL; GLYCERIN; GLYOXYLOYL CARBOCYSTEINE; ALOE VERA LEAF; BIOTIN; ARGAN OIL

81653-007 Update

Active Ingredient

Minoxidil 5% w/v

Purpose

Hair regrowth treatment

Use

to regrow hair

Warnings

For external use only.

Do not use if:

You are a pregnant woman

Your amount of hair loss is different than that shown on the sideof this carton or your hair loss is on the front of the scalp. 5%minoxidil topical foam is not intended for frontal baldness orreceding hairline.

You suffer from metal allergies

You have no family history of hair loss.

You hair loss is sudden and/or patchy.

You do not know the reason for your hair loss.

You are under 18 years of age. Do not use on babies and children.

You scalp is red, inflamed, infected, irritated, or painful.

You use other medicines on the scalp.

Ask a doctor before use if

you have heart disease

When using this product:

Do not apply on other parts of the body

Avoid contact with the eyes. In case of accidental contact, rinse

eyes with large amounts of cool tap water.

Some people have experienced changes in hair color and/or texture.

It takes time to regrow hair. Results may occur at 2 months withtwice a day usage. For some people, you may need to use thisproduct for at least 4 months before you see results.The amount of hair regrowth is different for each person. Thisproduct will not work for all people.

Stop use and ask a doctor if:

Chest pain, rapid heartbeat, faintness, or dizziness occurs.

Sudden, unexplained weight gain occurs.

Your hands or feet swell.

Scalp irritation or redness occurs.

Unwanted facial hair growth occurs

You do not see hair regrowth in 4 months.

May be harmful if used when pregnant or breast-feeding

Keep out of reach of children.

lf swallowed, get medical help orcontact Poison Control Center right away.

Directions

Men: Apply half a capful 2 times a day to the hair loss area.

Women: Apply half a capful 1 time a day to the hair loss area.

Massage to area with fingers, then wash hands well.

Using more and more often will not improve results.

Other information:

Hair growth has been shown in a clinical study of men (mostly
white) aged 18-49 years who used it for 4 months.
Store at controlled room temperature 20° to 25° C (68° to 77° Fcontents under pressure. Do not puncture or incinerate container.Do not expose to heat or store at temperatures above 120°F(49°C)

Inactive Ingredient

Aqua, hyaluronic acid, cocamidopropyl betaine, keratin aminoacids, tocopherol(vitamin E), glycerol, xanthan gum, glyoxyloylallantoin, aloe barbadensis leaf extract, propylene glycol, vitasvinifera seed extract, polygonum cuspidatum extract,ethylhexlglycerin, biotin, argania spinosa kernel oil, simmondsiachinesis (jojoba) seed oil, castor oil, saw palmetto, peppermint oil.rosemary oil, pumpkin seed oil, caffeine, stinging nettle,niancinimide, green tea